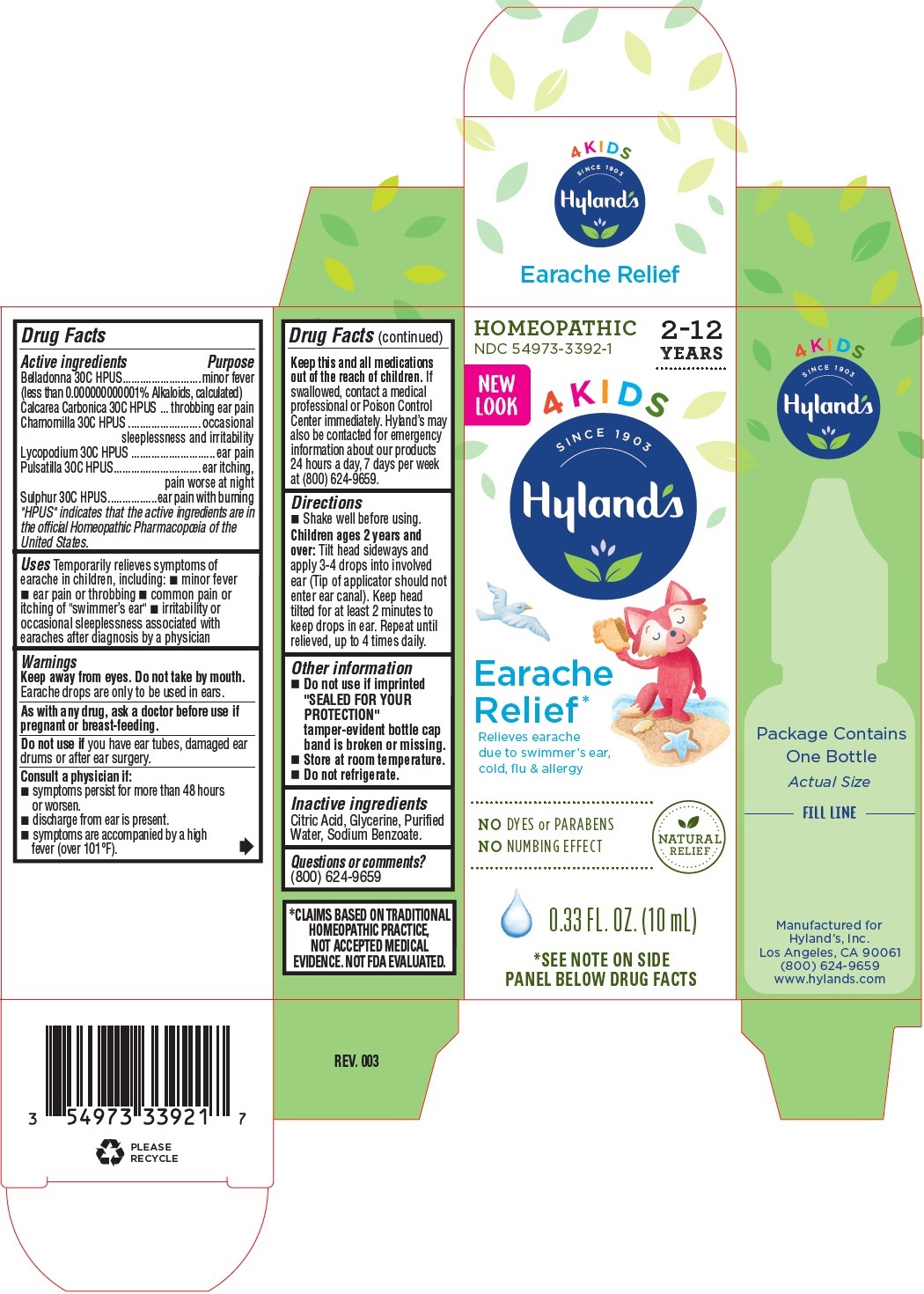 DRUG LABEL: 4 Kids Earache Relief
NDC: 54973-3392 | Form: LIQUID
Manufacturer: Hyland’s
Category: homeopathic | Type: HUMAN OTC DRUG LABEL
Date: 20221122

ACTIVE INGREDIENTS: ATROPA BELLADONNA 30 [hp_C]/1 mL; OYSTER SHELL CALCIUM CARBONATE, CRUDE 30 [hp_C]/1 mL; MATRICARIA CHAMOMILLA 30 [hp_C]/1 mL; ANEMONE PULSATILLA 30 [hp_C]/1 mL; SULFUR 30 [hp_C]/1 mL; LYCOPODIUM CLAVATUM SPORE 30 [hp_C]/1 mL
INACTIVE INGREDIENTS: WATER; CITRIC ACID MONOHYDRATE; GLYCERIN; SODIUM BENZOATE

4 Kids Earache Relief

Purpose

Relieves earache due to swimmer’s ear, cold, flu & allergy

Drug Facts

Active ingredients | Purpose
Belladonna 30C HPUS; (less than 0.000000000001% Alkaloids, calculated) | minor fever
Calcarea Carbonica 30C HPUS | throbbing ear pain
Chamomilla 30C HPUS | occasional sleeplessness and irritability
Lycopodium 30C HPUS | ear pain
Pulsatilla 30C HPUS | ear itching, pain worse at night
Sulphur 30C HPUS | ear pain with burning

"HPUS" indicates that the active ingredients are in the official Homeopathic Pharmacopœia of the United States.

Uses

Temporarily relieves symptoms of earache in children, including: ■ minor fever ■ ear pain or throbbing ■ common pain or

itching of "swimmer’s ear" ■ irritability or occasional sleeplessness associated with earaches after diagnosis by a physician

Warnings

Keep away from eyes. Do not take by mouth.

Earache drops are only to be used in ears.

PREGNANCY OR BREAST FEEDING

As with any drug, ask a doctor before use if pregnant or breast-feeding.

Do not use if you have ear tubes, damaged ear drums or after ear surgery.

ASK DOCTOR/PHARMACIST

Consult a physician if: ■ symptoms persist for more than 48 hours or worsen. ■ discharge from ear is present. ■ symptoms are accompanied by a high fever (over 101°F).

Drug Facts (continued)

KEEP OUT OF REACH OF CHILDREN

Keep this and all medications out of the reach of children. If swallowed, contact a medical professional or Poison Control Center immediately. Hyland’s may also be contacted for emergency information about our products 24 hours a day, 7 days per week at (800) 624-9659.

Directions

■ Shake well before using.

Children ages 2 years and over: Tilt head sideways and apply 3-4 drops into involved ear (Tip of applicator should not enter ear canal). Keep head tilted for at least 2 minutes to keep drops in ear. Repeat until relieved, up to 4 times daily.

Other information

■ Do not use if imprinted "SEALED FOR YOUR PROTECTION" tamper-evident bottle cap band is broken or missing.

■ Store at room temperature.

■ Do not refrigerate.

Inactive ingredients

Citric Acid, Glycerine, Purified Water, Sodium Benzoate.

Questions or comments?

(800) 624-9659

Indications and Usage (Uses)

Temporarily relieves symptoms of earache in children, including: ■ minor fever ■ ear pain or throbbing ■ common pain or

itching of "swimmer’s ear" ■ irritability or occasional sleeplessness associated with earaches after diagnosis by a physician

Dosage and Administration (Directions)

■ Shake well before using.

Children ages 2 years and over: Tilt head sideways and apply 3-4 drops into involved ear (Tip of applicator should not enter ear canal). Keep head tilted for at least 2 minutes to keep drops in ear. Repeat until relieved, up to 4 times daily.

Principal Display Panel

HOMEOPATHIC

NDC 54973-3392-1

2-12

YEARS

NEW

LOOK

4 KIDS

SINCE 1903

Hyland's

Earache

Relief*

Relieves earache

due to swimmer’s ear,

cold, flu & allergy

NO DYES or PARABENS

NO NUMBING EFFECT

NATURAL

RELIEF*

0.33 FL. OZ. (10 mL)

*SEE NOTE ON SIDE

PANEL BELOW DRUG FACTS